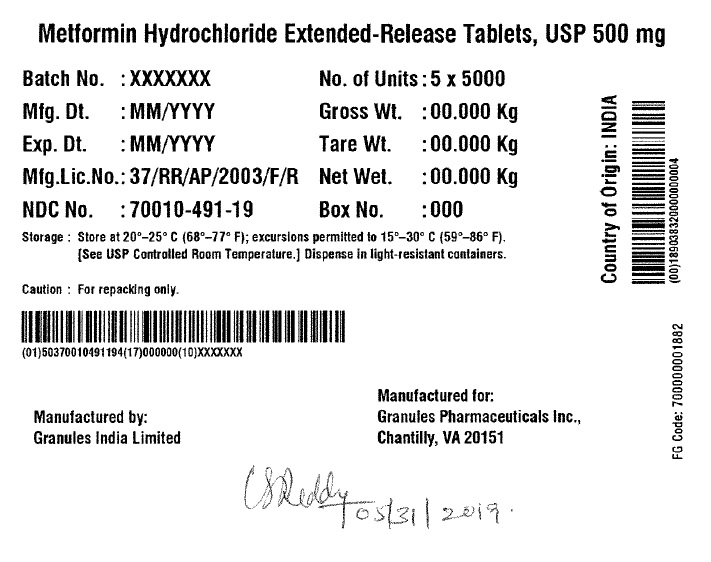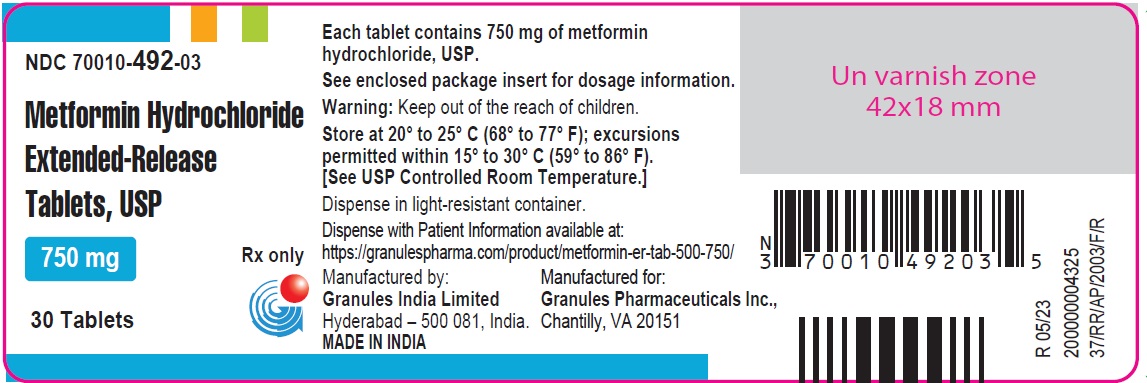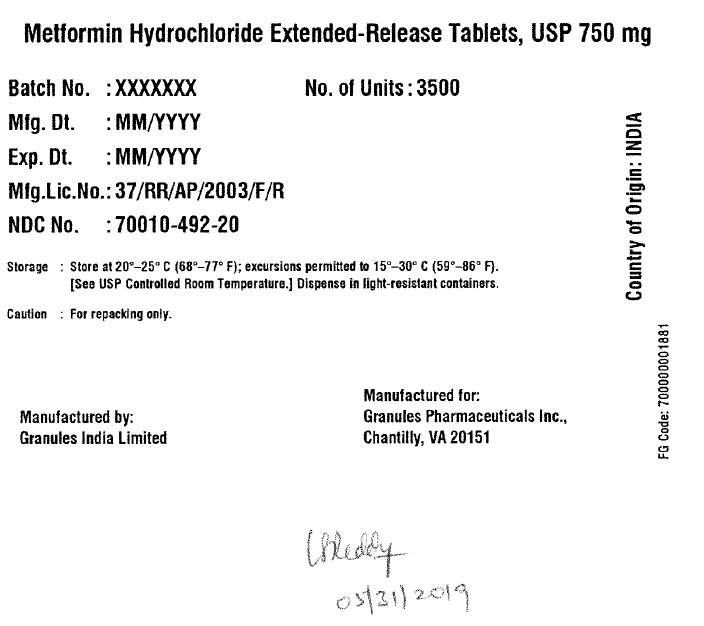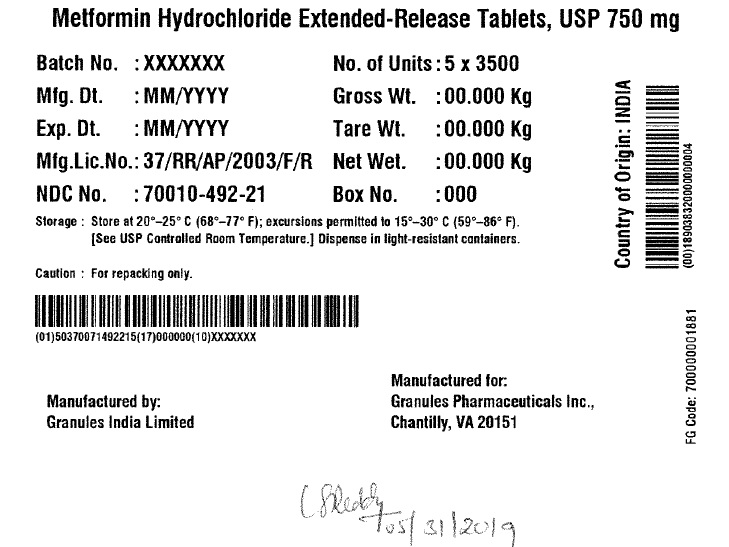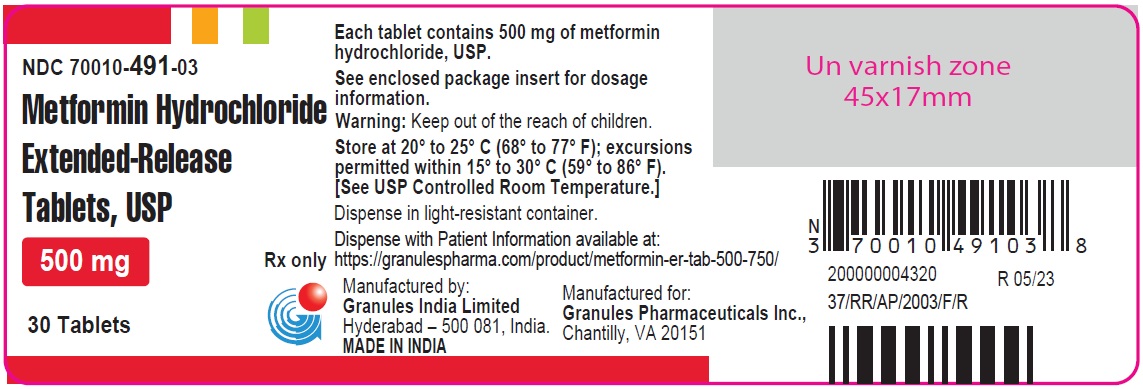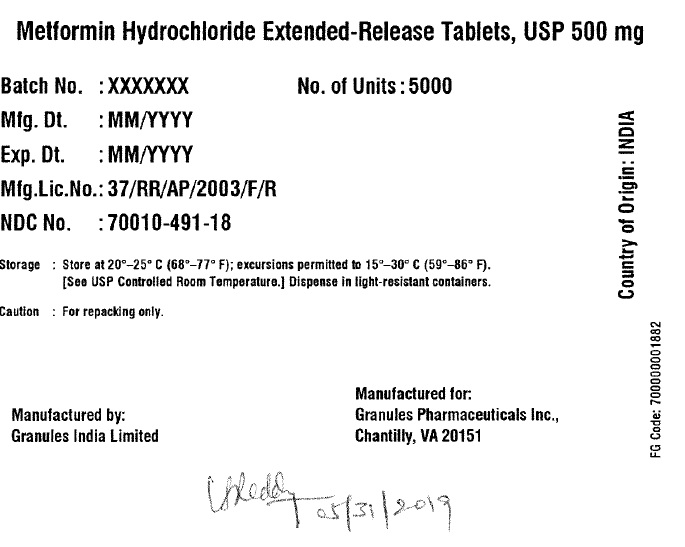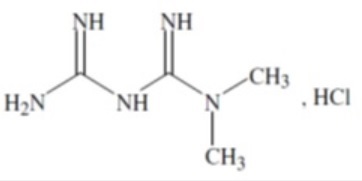 DRUG LABEL: Metformin
NDC: 70010-491 | Form: TABLET, EXTENDED RELEASE
Manufacturer: Granules Pharmaceuticals Inc.
Category: prescription | Type: HUMAN PRESCRIPTION DRUG LABEL
Date: 20251204

ACTIVE INGREDIENTS: METFORMIN HYDROCHLORIDE 500 mg/1 1
INACTIVE INGREDIENTS: HYPROMELLOSE 2208 (100 MPA.S); POVIDONE K30; HYPROMELLOSE 2910 (15 MPA.S); MAGNESIUM STEARATE

Metformin Hydrochloride Extended-Release Tablets 500 mg and 750 mg

DESCRIPTION

Metformin Hydrochloride Extended-Release Tablets, USP

Metformin hydrochloride extended-release tablets, USP are oral antihyperglycemic drugs used in the management of type 2 diabetes. Metformin hydrochloride, USP (N,N-dimethyl-monohydrochloride,Imidodicarbonimidic diamide) is not chemically or pharmacologically related to any other classes of oral antihyperglycemic agents. The structural formula is as shown:

Metformin hydrochloride, USP is a white or almost white, crystalline powder with a molecular formula of C4H11N5•HCl and a molecular weight of 165.62. Metformin hydrochloride is freely soluble in water, slightly soluble in alcohol, practically insoluble in acetone and in Methylene chloride. The pKa of metformin is 12.4. The pH of a 1% aqueous solution of metformin hydrochloride is 6.35.
Metformin hydrochloride extended-release tablets, USP contain 500 mg or 750 mg of metformin hydrochloride as the active ingredient.
Metformin hydrochloride extended-release tablets, USP 500 mg and 750 mg tablets contain the inactive ingredients hypromellose, magnesium stearate, and polyvinyl pyrrolidone.
Dissolution Method: Test 10
System Components and Performance - Metformin hydrochloride extended-release tablets, USP comprises a dual hydrophilic polymer matrix system. Metformin hydrochloride, USP is combined with a drug release controlling polymer to form an "inner" phase, which is then incorporated as discrete particles into an "external" phase of a second polymer. After administration, fluid from the gastrointestinal (GI) tract enters the tablet, causing the polymers to hydrate and swell. Drug is released slowly from the dosage form by a process of diffusion through the gel matrix that is essentially independent of pH. The hydrated polymer system is not rigid and is expected to be broken up by normal peristalsis in the GI tract. The biologically inert components of the tablet may occasionally remain intact during GI transit and will be eliminated in the feces as a soft, hydrated mass.

CLINICAL PHARMACOLOGY

Mechanism of Action

Metformin is an antihyperglycemic agent which improves glucose tolerance in patients with type 2 diabetes, lowering both basal and postprandial plasma glucose. Its pharmacologic mechanisms of action are different from other classes of oral antihyperglycemic agents. Metformin decreases hepatic glucose production, decreases intestinal absorption of glucose, and improves insulin sensitivity by increasing peripheral glucose uptake and utilization. Unlike sulfonylureas, metformin does not produce hypoglycemia in either patients with type 2 diabetes or normal subjects (except in special circumstances, see PRECAUTIONS) and does not cause hyperinsulinemia. With metformin therapy, insulin secretion remains unchanged while fasting insulin levels and day-long plasma insulin response may actually decrease.

Pharmacokinetics

Absorption and Bioavailability

Following a single oral dose of Metformin Hydrochloride Extended-Release Tablets, Cmax is achieved with a median value of 7 hours and a range of 4 to 8 hours.Peak plasma levels are approximately 20% lower compared to the same dose of metformin hydrochloride tablets, however, the extent of absorption (as measured by AUC) is similar to metformin hydrochloride tablets.
At steady state, the AUC and Cmax are less than dose proportional for metformin hydrochloride extended-release tablets within the range of 500 to 2000 mg administered once daily. Peak plasma levels are approximately 0.6, 1.1, 1.4, and 1.8 mcg/mL for 500, 1000, 1500, and 2000 mg once-daily doses, respectively. The extent of metformin absorption (as measured by AUC) from metformin hydrochloride extended-release tablets at a 2000 mg once-daily dose is similar to the same total daily dose administered as metformin hydrochloride tablets 1000 mg twice daily. After repeated administration of metformin hydrochloride extended-release tablets, metformin did not accumulate in plasma.
Within-subject variability in Cmax and AUC of metformin from metformin hydrochloride extended-release tablets is comparable to that with metformin hydrochloride tablets.
Although the extent of metformin absorption (as measured by AUC) from the metformin hydrochloride extended-release tablets increased by approximately 50% when given with food, there was no effect of food on Cmax and Tmax of metformin. Both high and low fat meals had the same effect on the pharmacokinetics of metformin hydrochloride extended-release tablets.
Distribution
The apparent volume of distribution (V/F) of metformin following single oral doses of metformin hydrochloride 850 mg averaged 654 ± 358 L. Metformin is negligibly bound to plasma proteins, in contrast to sulfonylureas, which are more than 90% protein bound. Metformin partitions into erythrocytes, most likely as a function of time. At usual clinical doses and dosing schedules of metformin hydrochloride tablets, steady state plasma concentrations of metformin are reached within 24 to 48 hours and are generally <1 mcg/mL. During controlled clinical trials of metformin hydrochloride tablets, maximum metformin plasma levels did not exceed 5 mcg/mL, even at maximum doses.

Metabolism and Elimination

Intravenous single-dose studies in normal subjects demonstrate that metformin is excreted unchanged in the urine and does not undergo hepatic metabolism (no metabolites have been identified in humans) nor biliary excretion. Renal clearance (see Table 1) is approximately 3.5 times greater than creatinine clearance, which indicates that tubular secretion is the major route of metformin elimination. Following oral administration, approximately 90% of the absorbed drug is eliminated via the renal route within the first 24 hours, with a plasma elimination half-life of approximately 6.2 hours. In blood, the elimination half-life is approximately 17.6 hours, suggesting that the erythrocyte mass may be a compartment of distribution.

Specific Population

Patients with Type 2 Diabetes

In the presence of normal renal function, there are no differences between single- or multiple-dose pharmacokinetics of metformin between patients with type 2 diabetes and normal subjects (see Table 1) nor is there any accumulation of metformin in either group at usual clinical doses.

The pharmacokinetics of metformin hydrochloride extended-release tablets in patients with type 2 diabetes is comparable to those in healthy normal adults.

Renal Impairment

In patients with decreased renal function (based on measured creatinine clearance), the plasma and blood half-life of metformin is prolonged and the renal clearance is decreased in proportion to the decrease in creatinine clearance (see Table 1: also see also see CONTRAINDICATIONS, WARNINGS, PRECAUTIONS, and DOSAGE AND ADMINISTRATION).

Hepatic Impairment

No parmacokinetic studies of metformin have been conducted in patients with hepatic insufficiency (see PRECAUTIONS).

Geriatrics

Limited data from controlled pharmacokinetic studies of metformin hydrochloride tablets in healthy elderly subjects suggest that total plasma clearance of metformin is decreased, the half-life is prolonged, and Cmax is increased, compared to healthy young subjects. From these data, it appears that the change in metformin pharmacokinetics with aging is primarily accounted for by a change in renal function (see Table 1; also see WARNINGS, PRECAUTIONS, and DOSAGE AND ADMINISTRATION). Metformin hydrochloride extended-release tablets treatment should not be initiated in patients ≥80 years of age unless measurement of creatinine clearance demonstrates that renal function is not reduced (see WARNINGS and DOSAGE AND ADMINISTRATION).

Table 1: Select Mean (± S.D.) Metformin Pharmacokinetic Parameters Following Single or Multiple Oral Doses of Metformin Hydrochloride Tablets
Subject Groups: Metformin Hydrochloride Tablet dosea (number of subjects) | Cmaxb (mcg/mL) | Tmaxc (hrs) | Renal Clearance (mL/min)
Healthy, nondiabetic adults:
500 mg single dose (24) | 1.03 (±0.33) | 2.75 (±0.81) | 600 (±132)
850 mg single dose (74)d | 1.60 (±0.38) | 2.64 (±0.82) | 552 (±139)
850 mg three times daily for 19 dosese (9) | 2.01 (±0.42) | 1.79 (±0.94) | 642 (±173)
Adults with type 2 diabetes:
850 mg single dose (23) | 1.48 (±0.5) | 3.32 (±1.08) | 491 (±138)
850 mg three times daily for 19 dosese (9) | 1.90 (±0.62) | 2.01 (±1.22) | 550 (±160)
Elderlyf , healthy nondiabetic adults:
850 mg single dose (12) | 2.45 (±0.70) | 2.71 (±1.05) | 412 (±98)
Renal-impaired adults:
850 mg single dose
Mild (CLcrg 61-90 mL/min) (5) | 1.86 (±0.52) | 3.20 (±0.45) | 384 (±122)
Moderate (CLcr 31-60 mL/min) (4) | 4.12 (±1.83) | 3.75 (±0.50) | 108 (±57)
Severe (CLcr 10-30 mL/min) (6) | 3.93 (±0.92) | 4.01 (±1.10) | 130 (±90)

a All doses given fasting except the first 18 doses of the multiple dose studies

b Peak plasma concentration

c Time to peak plasma concentration

d Combined results (average means) of five studies: mean age 32 years (range 23-59 years)

e Kinetic study done following dose 19, given fasting

f Elderly subjects, mean age 71 years (range 65-81 years)

g CLcr = creatinine clearance normalized to body surface area of 1.73 m^2

Gender
Metformin pharmacokinetic parameters did not differ significantly between normal subjects and patients with type 2 diabetes when analyzed according to gender (males = 19, females = 16).
Race

No studies of metformin pharmacokinetic parameters according to race have been performed.

Clinical Studies

Metformin Hydrochloride Extended-Release Tablets

A 24-week, double-blind, placebo-controlled study of metformin hydrochloride extended-release tablets, taken once daily with the evening meal, was conducted in patients with type 2 diabetes who had failed to achieve glycemic control with diet and exercise (HbA1c 7 to 10%, FPG 126 to 270 mg/dL). Patients entering the study had a mean baseline HbA1c of 8% and a mean baseline FPG of 176 mg/dL. After 12 weeks treatment, mean HbA1c had increased from baseline by 0.1% and mean FPG decreased from baseline by 2 mg/dL in the placebo group, compared with a decrease in mean HbA1c of 0.6% and a decrease in mean FPG of 23 mg/dL in patients treated with metformin hydrochloride extended-release tablets 1000 mg once daily. Subsequently, the treatment dose was increased to 1500 mg once daily if HbA1c was ≥7% but <8% (patients with HbA1c ≥8% were discontinued from the study). At the final visit (24-week), mean HbA1c had increased 0.2% from baseline in placebo patients and decreased 0.6% with metformin hydrochloride extended-release tablets.

A 16-week, double-blind, placebo-controlled, dose-response study of metformin hydrochloride extended-release tablets, taken once daily with the evening meal or twice daily with meals, was conducted in patients with type 2 diabetes who had failed to achieve glycemic control with diet and exercise (HbA1c 7 to 11%, FPG 126 to 280 mg/dL). Changes in glycemic control and body weight are shown in Table 2.

Table 2:Sum mary of Mean Ch a nges f rom Baseline* in Hb A1c, Fasting Plasma Glucose, and Body Weight at Final Visit (16-week study)
 | Metformin Hydrochloride Extended–Release Tablets |  |  |  |  | Placebo
 | 500 mg once Daily | 1000 mg once Daily | 1500 mg once Daily | 2000 mg once Daily | 1000 mg Twice Daily | Placebo
Hemoglobin A1c (%) Baseline Change at FINAL VISIT p-valuea | (n=115) 8.2 -0.4 <0.001 | (n=115) 8.4 -0.6 <0.001 | (n=111) 8.3 -0.9 <0.001 | (n=125) 8.4 -0.8 <0.001 | (n=112) 8.4 -1.1 <0.001 | (n=111) 8.4 0.1 -
FPG (mg/dL) Baseline Change at FINAL VISIT p-valuea | (n=126) 182.7 -15.2 <0.001 | (n=118) 183.7 -19.3 <0.001 | (n=120) 178.9 -28.5 <0.001 | (n=132) 181 -29.9 <0.001 | (n=122) 181.6 -33.6 <0.001 | (n=113) 179.6 7.6 -
Body Weight (lbs) Baseline Change at FINAL VISIT p-valuea | (n=125) 192.9 -1.3 NS** | (n=119) 191.8 -1.3 NS** | (n=117) 188.3 -0.7 NS** | (n=131) 195.4 -1.5 NS** | (n=119) 192.5 -2.2 NS** | (n=113) 194.3 -1.8 -

*All patients on diet therapy at Baseline

a All comparisons versus Placebo

**Not statistically significant

Compared with placebo, improvement in glycemic control was seen at all dose levels of metformin hydrochloride extended-release tablets and treatment was not associated with any significant change in weight (see DOSAGE AND ADMINISTRATION) for dosing recommendations for metformin hydrochloride extended-release tablets.

A 24-week, double-blind, randomized study of metformin hydrochloride extended-release tablets, taken once daily with the evening meal, and metformin hydrochloride tablets, taken twice daily (with breakfast and evening meal), was conducted in patients with type 2 diabetes who had been treated with metformin hydrochloride 500 mg twice daily for at least 8 weeks prior to study entry.

The metformin hydrochloride dose had not necessarily been titrated to achieve a specific level of glycemic control prior to study entry. Patients qualified for the study if HbA1c was ≤8.5% and FPG was ≤200 mg/dL. Changes in glycemic control and body weight are shown in Table 3.

Table3: Summary of Mean Changes from Baseline* in HbA1c, Fasting Plasma Glucose, and Body Weight at Week 12 and at Final Visit (24-week study)
 | Metformin Hydrochloride Tablets 500 mg Twice Daily | Metformin Hydrochloride Extended-Release Tablets
 | Metformin Hydrochloride Tablets 500 mg Twice Daily | 1000 mg Once Daily | 1500 mg Once Daily
Hemoglobin A1c (%) | (n=67) | (n=72) | (n=66)
Baseline | 7.06 | 6.99 | 7.02
Change at 12 Weeks | 0.14 | 0.23 | 0.04
(95% CI) | (-0.03, 0.31) | (0.10, 0.36) | (-0.08, 0.15)
Change at FINAL VISIT | 0.14a | 0.27 | 0.13
(95% CI) | (-0.04, 0.31) | (0.11, 0.43) | (-0.02, 0.28)
FPG (mg/dL) | (n=69) | (n=72) | (n=70)
Baseline | 127.2 | 131 | 131.4
Change at 12 Weeks | 12.9 | 9.5 | 3.7
(95% CI) | (6.5, 19.4) | (4.4, 14.6) | (-0.4, 7.8)
Change at FINAL VISIT | 14 | 11.5 | 7.6
(95% CI) | (7, 21) | (4.4, 18.6) | (1.0, 14.2)
Body Weight (lbs) | (n=71) | (n=74) | (n=71)
Baseline | 210.3 | 202.8 | 192.7
Change at 12 Weeks | 0.4 | 0.9 | 0.7
(95% CI) | (-0.4, 1.5) | (0.0, 2) | (-0.4, 1.8)
Change at FINAL VISIT | 0.9 | 1.1 | 0.9
(95% CI) | (-0.4, 2.2) | (-0.2, 2.4) | (-0.4, 2)

* All patients on metformin hydrochloride tablets 500 mg twice daily at Baseline

a n=68

After 12 weeks of treatment, there was an increase in mean HbA1c in all groups; in the metformin hydrochloride extended-release tablets 1000 mg group, the increase from baseline of 0.23% was statistically significant (see DOSAGE AND ADMINISTRATION).

Changes in lipid parameters in the previously described placebo-controlled dose-response study of metformin hydrochloride extended-release tablets are shown in Table 4.

Table 4:Summary of Mean Percent Changes from Baseline* in Major Lipid Variables at Final Visit (16-week study)
 | Metformin Hydrochloride Extended–Release Tablets |  |  |  |  | Placebo
 | 500 mg once Daily | 1000 mg once Daily | 1500 mg once Daily | 2000 mg once Daily | 1000 mg Twice Daily | Placebo
Total Cholesterol (mg/dL) Baseline Mean % Change at FINAL VISIT | (n=120) 210.3 1% | (n=113) 218.1 1.7% | (n=110) 214.6 0.7% | (n=126) 204.4 -1.6% | (n=117) 208.2 -2.6% | (n=110) 208.6 -2.6%
Total Triglyceides (mg/dL) Baseline Mean % Change at FINAL VISIT | (n=120) 220.2 14.5% | (n=113) 211.9 9.4% | (n=110) 198 15.1% | (n=126) 194.2 14.9% | (n=117) 179 9.4% | (n=110) 211.7 10.9%
LDL Cholesterol (mg/dL) Baseline Mean % Change at FINAL VISIT | (n=119) 131 -1.4% | (n=113) 134.9 -1.6% | (n=109) 135.8 -3.5% | (n=126) 125.8 -3.3% | (n=117) 131.4 -5.5% | (n=107) 131.9 -3.2%
HDL Cholesterol (mg/dL) Baseline Mean % Change at FINAL VISIT | (n=120) 40.8 6.2% | (n=108) 41.6 8.6% | (n=108) 40.6 5.5% | (n=125) 40.2 6.1% | (n=117) 42.4 7.1% | (n=108) 39.4 5.8%

*All patients on diet therapy at Baseline

Changes in lipid parameters in the previously described study of metformin hydrochloride tablets and metformin hydrochloride extended-release tablets are shown in Table 5.

Table 5: Summary of Mean Percent Changes from Baseline* in Major Lipid Variables at Final Visit (24 week study)
 | Metformin Hydrochloride Tablets 500 mg Twice Daily | Metformin Hydrochloride Extended-Release Tablets
 | Metformin Hydrochloride Tablets 500 mg Twice Daily | 1000 mg Once Daily | 1500 mg Once Daily
Total Cholesterol (mg/dL) | (n=68) | (n=70) | (n=66)
Baseline | 199 | 201.9 | 201.6
Mean % Change at FINAL VISIT | 0.1% | 1.3% | 0.1%
Total Triglycerides (mg/dL) | (n=68) | (n=70) | (n=66)
Baseline | 178 | 169.2 | 206.8
Mean % Change at FINAL VISIT | 6.3% | 25.3% | 33.4%
LDL-Cholesterol (mg/dL) | (n=68) | (n=70) | (n=66)
Baseline | 122.1 | 126.2 | 115.7
Mean % Change at FINAL VISIT | -1.3% | -3.3% | -3.7%
HDL-Cholesterol (mg/dL) | (n=68) | (n=70) | (n=65)
Baseline | 41.9 | 41.7 | 44.6
Mean % Change at FINALVISIT | 4.8% | 1% | -2.1%

*All patients on metformin hydrochloride tablets 500 mg twice daily at baseline

INDICATIONS & USAGE

Metformin hydrochloride extended-release tablets, USP are indicated as an adjunct to diet and exercise to improve glycemic control in patients with type 2 diabetes mellitus.

CONTRAINDICATIONS

Metformin hydrochloride extended-release tablets, USP are contraindicated in patients with:

1. Severe Renal Impairment (eGFR below 30mL/min/1.73m2) (see WARNINGS and PRECAUTIONS).

2.Known hypersensitivity to metformin hydrochloride, USP.

3.Acute or chronic metabolic acidosis, including diabetic ketoacidosis, with or without coma. Diabetic ketoacidosis should be treated with insulin.

WARNINGS

LACTIC ACIDOSIS:
Postmarketing cases of metformin-associated lactic acidosis have resulted in death, hypothermia, hypotension and resistant bradyarrhythmias. The onset of metformin associated lactic acidosis is often subtle, accompanied only by nonspecific symptoms such as malaise, myalgias, respiratory distress, somnolence, and abdominal pain. Metformin associated lactic acidosis was characterized by elevated blood lactate levels(>5 mmol/Liter), anion gap acidosis (without evidenceof ketonuria or ketonemia), an increased lactate/pyruvate ratio; and metformin plasma levels generally >5 mcg/mL (see PRECAUTIONS).
Risk factors for metformin associated lactic acidosis include renal impairment, concamitent use of certain drugs (e.g carbonic anhydrase inhibitors such as topiramate), age 65 years old or greater, having a radiological study with contrast, surgery and other procedures, hypoxic states (e.g., acute congestive heart failure), excessive alcohol intake, and hepatic impairment.
Steps to reduce the risk of and manage metformin-associated lactic acidosis in these high risk groups are provided (see DOSAGE AND ADMINISTRATION, CONTRAINDICATIONS, AND PRECAUTIONS).
If metformin associated lactic acidosis is suspected, immediately discontinue metformin hydrochloride extend release tablets and institute general supportive measures in a hospital setting. Prompt hemodialysis is recommended (see PRECAUTIONS).

PRECAUTIONS

General Precautions

• Lactic acidosis –There have been post marketing cases of metformin-associated lactic acidosis, including fatal cases. These cases had a subtle onset and were accompanied by
nonspecific symptoms such as malaise, myalgias, abdominal pain, respiratory distress, or increased somnolence; however, hypotension and resistant bradyarrhythmias have
occurred with severe acidosis. Metformin-associated lactic acidosis was characterized by elevated blood lactate concentrations (>5 mmol/L), anion gap acidosis (without evidence
of ketonuria or ketonemia), and an increased lactate: pyruvate ratio; metformin plasma levels were generally >5 mcg/mL. Metformin decreases liver uptake of lactate increasing
lactate blood levels which may increase the risk of lactic acidosis, especially in patients at risk.
If metformin-associated lactic acidosis is suspected, general supportive measures should be instituted promptly in a hospital setting, along with immediate discontinuation of or
metformin hydrochloride extend release tablets. In metformin hydrochloride extend release tablets treated patients with a diagnosis or strong suspicion of lactic acidosis, prompt
hemodialysis is recommended to correct the acidosis and remove accumulated metformin (metformin hydrochloride is dialyzable with a clearance of up to 170 mL/min under good
hemodynamic conditions). Hemodialysis has often resulted in reversal of symptoms and recovery.
Educate patients and their families about the symptoms of lactic acidosis and, if these symptoms occur, instruct them to discontinue metformin hydrochloride extend release
tablets and report these symptoms to their healthcare provider.
For each of the known and possible risk factors for metformin-associated lactic acidosis, recommendations to reduce the risk of and manage metformin-associated lactic acidosis
are provided below:
• Renal impairment—The post marketing metformin-associated lactic acidosis cases primarily occurred in patients with significant renal impairment.
The risk of metformin accumulation and metformin-associated lactic acidosis increases with the severity of renal impairment because metformin is substantially excreted by the
kidney. Clinical recommendations based upon the patient’s renal function include (see DOSAGE AND ADMINISTRATION, CLINICAL PHARMACOLOGY):
o Before initiating metformin hydrochloride extend release tablets, obtain an estimated glomerular filtration rate (eGFR)
o Metformin hydrochloride extend release tablets is contraindicated in patients with an eGFR less than 30 mL/min/1.73 m2 (see CONTRAINDICATIONS).
o Initiation of metformin hydrochloride extend release tablets is not recommended in patients with eGFR between 30-45 mL/min/1.73 m2.
o Obtain an eGFR at least annually in all patients taking metformin hydrochloride extend release tablets. In patients at risk for the development of renal impairment (e.g., the
elderly), renal function should be assessed more frequently.
o In patients taking metformin hydrochloride extend release tablets whose eGFR falls below 45 mL/min/1.73 m2, assess the benefit and risk of continuing therapy.
• Drug Interactions – The concomitant use of metformin hydrochloride extend release tablets with specific drugs may increase the risk of metformin-associated lactic acidosis:
those that impair renal function, result in significant hemodynamic change, interfere with acid-base balance, or increase metformin accumulation. Consider more frequent
monitoring of patients.
• Age 65 or greater—The risk of metformin-associated lactic acidosis increases with the patient’s age because elderly patients have a greater likelihood of having hepatic, renal,
or cardiac impairment than younger patients. Assess renal function more frequently in elderly patients.
• Radiologic studies with contrast—Administration of intravascular iodinated contrast agents in metformin-treated patients has led to an acute decrease in renal function and the
occurrence of lactic acidosis. Stop metformin hydrochloride extended release tablets at the time of, or prior to, an iodinated contrast imaging procedure in patients with an eGFR
between 30 and 60 mL/min/1.73 m2; in patients with a history of hepatic impairment, alcoholism or heart failure; or in patients who will be administered intra-arterial iodinated
contrast. Re-evaluate eGFR 48 hours after the imaging procedure, and restart metformin hydrochloride extended release tablets if renal function is stable.
• Surgery and other procedures—withholding of food and fluids during surgical or other procedures may increase the risk for volume depletion, hypotension, and renal impairment.
Metformin hydrochloride extended-release tablets should be temporarily discontinued while patients have restricted food and fluid intake.
• Hypoxic states— several of the postmarketing cases of metformin-associated lactic acidosis occurred in the setting of acute congestive heart failure (particularly when
accompanied by hypoperfusion and hypoxemia). Cardiovascular collapse (shock), acute myocardial infarction, sepsis, and other conditions associated with hypoxemia have been
associated with lactic acidosis and may cause prerenal azotemia. When such an event occurs, discontinue metformin hydrochloride extended release tablets.

• Excessive alcohol intake—Alcohol is known to potentiate the effect of metformin on lactate metabolism. Patients, therefore, should be warned against excessive alcohol intake,
acute or chronic, while receiving metformin hydrochloride extended-release tablets.

• Hepatic impairment—Patients with hepatic impairment have developed cases of metformin associated lactic acidosis. This may be due to impaired lactate clearance resulting in
higher lactate blood levels. Therefore, avoid use of metformin hydrochloride extended release tablets in patients with clinical or laboratory evidence of hepatic disease.

Vitamin B12 levels— In controlled clinical trials of metformin of 29 weeks duration, a decrease to subnormal levels of previously normal serum vitamin B12 levels, without clinical manifestations, was observed in approximately 7% of patients. Such decrease, possibly due to interference with B12 absorption from the B12-intrinsic factor complex, is, however, very rarely associated with anemia and appears to be rapidly reversible with discontinuation of metformin or vitamin B12 supplementation. Measurement of hematologic parameters on an annual basis is advised in patients on metformin hydrochloride extended-release tablets and any apparent abnormalities should be appropriately investigated and managed (see P R ECAUTIONS: Laboratory Tests).

Certain individuals (those with inadequate vitamin B12 or calcium intake or absorption) appear to be predisposed to developing subnormal vitamin B12 levels. In these patients, routine serum vitamin B12 measurements at 2- to 3- year intervals may be useful.

Change in clinical status of patients with previously controlled type 2 diabetes—A patient with type 2 diabetes previously well controlled on metformin hydrochloride extended-release tablets who develops laboratory abnormalities or clinical illness (especially vague and poorly defined illness) should be evaluated promptly for evidence of ketoacidosis or lactic acidosis. Evaluation should include serum electrolytes and ketones, blood glucose and, if indicated, blood pH, lactate, pyruvate, and metformin levels. If acidosis of either form occurs, metformin hydrochloride extended-release tablets must be stopped immediately and other appropriate corrective measures initiated (see also WARNINGS).

Hypoglycemia—Hypoglycemia does not occur in patients receiving metformin hydrochloride extended-release tablets alone under usual circumstances of use, but could occur when caloric intake is deficient, when strenuous exercise is not compensated by caloric supplementation, or during concomitant use with other glucose-lowering agents (such as sulfonylureas and insulin) or ethanol.

Elderly, debilitated, or malnourished patients, and those with adrenal or pituitary insufficiency or alcohol intoxication are particularly susceptible to hypoglycemic effects. Hypoglycemia may be difficult to recognize in the elderly, and in people who are taking beta-adrenergic blocking drugs.

Macrovascular Outcomes—There have been no clinical studies establishing conclusive evidence of macrovascular risk reduction with metformin hydrochloride extended-release tablets or any other anti-diabetic drug.

Information for Patients

Patients should be informed of the potential risks and benefits of metformin hydrochloride extended-release tablets and of alternative modes of therapy. They should also be informed about the importance of adherence to dietary instructions, of a regular exercise program, and of regular testing of blood glucose, glycosylated hemoglobin, renal function, and hematologic parameters.
The risks of lactic acidosis, its symptoms, and conditions that predispose to its development, as noted in the WARNINGS

and PRECAUTIONS sections, should be explained to patients. Patients should be advised to discontinue metformin hydrochloride extended-release tablets immediately and to promptly notify their health practitioner if unexplained hyperventilation, myalgia, malaise, unusual somnolence, or other nonspecific symptoms occur. Once a patient is stabilized on any dose level of metformin hydrochloride extended-release tablets, gastrointestinal symptoms, which are common during initiation of metformin therapy, are unlikely to be drug related. Later occurrence of gastrointestinal symptoms could be due to lactic acidosis or other serious disease.
Patients should be counselled against excessive alcohol intake, either acute or chronic, while receiving metformin hydrochloride extended-release tablets.
Metformin hydrochloride extended-release tablets alone does not usually cause hypoglycemia, although it may occur when metformin hydrochloride extended-release tablets is used in conjunction with oral sulfonylureas and insulin. When initiating combination therapy, the risks of hypoglycemia, its symptoms and treatment, and conditions that predispose to its development should be explained to patients and responsible family members. (See Patient Information

printed below.)
Patients should be informed that metformin hydrochloride extended-release tablets must be swallowed whole and not crushed or chewed, and that the inactive ingredients may occasionally be eliminated in the feces as a soft mass that may resemble the original tablet.

Laboratory Tests

Response to all diabetic therapies should be monitored by periodic measurements of fasting blood glucose and glycosylated hemoglobin levels, with a goal of decreasing these levels toward the normal range. During initial dose titration, fasting glucose can be used to determine the therapeutic response. Thereafter, both glucose and glycosylated hemoglobin should be monitored. Measurements of glycosylated hemoglobin may be especially useful for evaluating long-term control (see also DOSAGE AND ADMINISTRATION).

Initial and periodic monitoring of hematologic parameters (e.g., hemoglobin/hematocrit and red blood cell indices) and renal function (serum creatinine) should be performed, at least on an annual basis.While megaloblastic anemia has rarely been seen with metformin hydrochloride therapy, if this is suspected, vitamin B12 deficiency should be excluded.
Instruct patients to inform their doctor that they are taking metformin hydrochloride extended-release tablets prior to any surgical or radiological procedure, as temporary discontinuation of metformin hydrochloride extended-release tablets may be required until renal function has been confirmed to be normal (see PRECAUTIONS).

Drug Interactions (Clinical Evaluation of Drug Interactions Conducted with Metformin hydrochloride)

Glyburide—In a single-dose interaction study in type 2 diabetes patients, coadministration of metformin and glyburide did not result in any changes in either metformin pharmacokinetics or pharmacodynamics. Decreases in glyburide AUC and Cmax were observed, but were highly variable. The single-dose nature of this study and the lack of correlation between glyburide blood levels and pharmacodynamic effects, makes the clinical significance of this interaction uncertain (see DOSAGE AND ADMINISTRATION: Concomitant metformin hydrochloride extended-release tablets and Oral Sulfonylurea Therapy in Adult Patients).

Furosemide—A single-dose, metformin-furosemide drug interaction study in healthy subjects demonstrated that pharmacokinetic parameters of both compounds were affected by coadministration. Furosemide increased the metformin plasma and blood Cmax by 22% and blood AUC by 15%, without any significant change in metformin renal clearance. When administered with metformin, the Cmax and AUC of furosemide were 31% and 12% smaller, respectively, than when administered alone, and the terminal half-life was decreased by 32%, without any significant change in furosemide renal clearance. No information is available about the interaction of metformin and furosemide when coadministered chronically.

Nifedipine—A single-dose, metformin-nifedipine drug interaction study in normal healthy volunteers demonstrated that co-administration of nifedipine increased plasma metformin Cmax and AUC by 20% and 9%, respectively, and increased the amount excreted in the urine. Tmax and half-life were unaffected. Nifedipine appears to enhance the absorption of metformin. Metformin had minimal effects on nifedipine.

Drugs that reduce metformin clearance—Concomitant use of drugs that interfere with common renal tubular transport systems involved in the renal elimination of metformin (e.g., organic cationic transporter-2 [OCT2] / multidrug and toxin extrusion [MATE] inhibitors such as ranolazine, vandetanib, dolutegravir, and cimetidine) could increase systemic exposure to metformin and may increase the risk for lactic acidosis. Consider the benefits and risks of concomitant use. Such interaction between metformin and oral cimetidine has been observed in normal healthy volunteers in both single- and multiple-dose, metformin-cimetidine drug interaction studies, with a 60% increase in peak metformin plasma and whole blood concentrations and a 40% increase in plasma and whole blood metformin AUC. There was no change in elimination half-life in the single-dose study. Metformin had no effect on cimetidine pharmacokinetics. Although such interactions remain theoretical (except for cimetidine), careful patient monitoring and dose adjustment of metformin hydrochloride extended-release tablets and/or the interfering drug is recommended in patients who are taking cationic medications that are excreted via the proximal renal tubular secretory system.

Other—Certain drugs tend to produce hyperglycemia and may lead to loss of glycemic control. These drugs include the thiazides and other diuretics, corticosteroids, phenothiazines, thyroid products, estrogens, oral contraceptives, phenytoin, nicotinic acid, sympathomimetics, calcium channel blocking drugs, and isoniazid. When such drugs are administered to a patient receiving metformin hydrochloride extended-release tablets, the patient should be closely observed for loss of blood glucose control. When such drugs are withdrawn from a patient receiving metformin hydrochloride extended-release tablets, the patient should be observed closely for hypoglycemia.

Carbonic anhydrase inhibitors—Topiramate or other carbonic anhydrase inhibitors (e.g., zonisamide, acetazolamide or dichlorphenamide) frequently cause a decrease in serum bicarbonate and induce non-anion gap, hyperchloremic metabolic acidosis. Concomitant use of these drugs with metformin hydrochloride extended-release tablets may increase the risk for lactic acidosis. Consider more frequent monitoring of these patients.

Alcohol—Alcohol is known to potentiate the effect of metformin on lactate metabolism. Warn patients against excessive alcohol intake while receiving metformin hydrochloride extended-release tablets.

Carcinogenesis, Mutagenesis, Impairment of Fertility

Long-term carcinogenicity studies have been performed in rats (dosing duration of 104 weeks) and mice (dosing duration of 91 weeks) at doses up to and including 900 mg/kg/day and 1500 mg/kg/day, respectively.

These doses are both approximately 4 times the maximum recommended human daily dose of 2000 mg based on body surface area comparisons. No evidence of carcinogenicity with metformin was found in either male or female mice. Similarly, there was no tumorigenic potential observed with metformin in male rats. There was, however, an increased incidence of benign stromal uterine polyps in female rats treated with 900 mg/kg/day.

There was no evidence of a mutagenic potential of metformin in the following in vitro tests: Ames test (S. typhimurium), gene mutation test (mouse lymphoma cells), or chromosomal aberrations test (human lymphocytes). Results in the in vivo mouse micronucleus test were also negative.

Fertility of male or female rats was unaffected by metformin when administered at doses as high as 600 mg/kg/day, which is approximately 3 times the maximum recommended human daily dose based on body surface area comparisons.

Pregnancy

Teratogenic Effects: Pregnancy Category B

Recent information strongly suggests that abnormal blood glucose levels during pregnancy are associated with a higher incidence of congenital abnormalities. Most experts recommend that insulin be used during pregnancy to maintain blood glucose levels as close to normal as possible. Because animal reproduction studies are not always predictive of human response, metformin hydrochloride extended-release tablets should not be used during pregnancy unless clearly needed.

There are no adequate and well-controlled studies in pregnant women with metformin hydrochloride extended-release tablets. Metformin was not teratogenic in rats and rabbits at doses up to 600 mg/kg/day. This represents an exposure of about 2 and 6 times the maximum recommended human daily dose of 2000 mg based on body surface area comparisons for rats and rabbits, respectively. Determination of fetal concentrations demonstrated a partial placental barrier to metformin.

Nursing Mothers

Studies in lactating rats show that metformin is excreted into milk and reaches levels comparable to those in plasma. Similar studies have not been conducted in nursing mothers. Because the potential for hypoglycemia in nursing infants may exist, a decision should be made whether to discontinue nursing or to discontinue the drug, taking into account the importance of the drug to the mother. If metformin hydrochloride extended-release tablets is discontinued, and if diet alone is inadequate for controlling blood glucose, insulin therapy should be considered.

Pediatric Use

Safety and effectiveness of metformin hydrochloride extended-release tablets in pediatric patients have not been established.

Geriatric Use

Controlled clinical studies of metformin hydrochloride extended-release tablets did not include sufficient numbers of elderly patients to determine whether they respond differently from younger patients, although other reported clinical experience has not identified differences in responses between the elderly and younger patients. In general, dose selection for an elderly patient should be cautious, usually starting at the low end of the dosing range, reflecting the greater frequency of decreased hepatic, renal, or cardiac function, and of concomitant disease or other drug therapy and the higher risk of lactic acidosis. Assess renal function more frequently in elderly patients (see WARNINGS, PRECAUTIONS, and DOSAGE AND ADMINISTRATION)

ADVERSE REACTIONS

In A US double blind clinical study of metformin hydrochloride tablets in patients with type 2 diabetes, a total of 141 patients received metformin hydrochloride tablets therapy (up to 2550 mg per day) and 145 patients received placebo. Adverse reactions reported in greater than 5% of the metformin hydrochloride tablets patients, and that were more common in metformin hydrochloride tablets than placebo treated patients, are listed in Table 6.

Table 6: Most Common Adverse Reactions (>5 Percent) in a Placebo-Controlled Clinical Study of Metformin Hydrochloride Tablets Monotherapy*
Adverse Reaction | Metformin Hydrochloride Tablets (n=141) | Placebo; (n=145)
Adverse Reaction | % of Patients | Placebo; (n=145)
Diarrhea | 53.2 | 11.7
Nausea/Vomiting | 25.5 | 8.3
Flatulence | 12.1 | 5.5
Asthenia | 9.2 | 5.5
Indigestion | 7.1 | 4.1
Abdominal Discomfort | 6.4 | 4.8
Headache | 5.7 | 4.8

*Reactions that were more common in metformin hydrochloride tablets than placebo treated patients.

Diarrhea led to discontinuation of study medication in 6% of patients treated with metformin hydrochloride tablets. Additionally, the following adverse reactions were reported in ≥1 - ≤5% of metformin hydrochloride tablets patients and myalgia, lightheaded, dyspnea, nail disorder, rash, sweating increased, taste disorder, chest discomfort, chills, flu syndrome, flushing, and palpitation.

In worldwide clinical trials over 900 patients with type 2 diabetes have been treated with metformin hydrochloride extended-release tablets in placebo and active controlled studies. In placebo controlled trails, 781 patients were administered metformin hydrochloride extended-release tablets and 195 patients received placebo. Adverse reactions reported in greater than 5% of the metformin hydrochloride extended release tablets patients, and that were more common in metformin hydrochloride extended-release tablets than placebo treated patients are listed in Table 7.

Table 7: Most Common Adverse Reactions (>5 Percent) in Placebo-Controlled Studies of Metformin Hydrochloride Extended-Release Tablets*
 | Metformin Hydrochloride Extended-Release Tablets(N=781) | Placebo; (N=195)
Adverse Reactions | % of patients
Diarrhea | 9.6 | 2.6
Nausea/Vomiting | 6.5 | 1.5

Diarrhea led to discontinuation of study medication in 0.6% of patients treated with metformin hydrochloride extended-release tablets. Additionally, the following adverse reactions were reported in ≥1 - ≤5% of metformin hydrochloride extended-release tablets patients and were more commonly reported with metformin hydrochloride extended-release tablets than placebo: abdominal pain, constipation, distention abdomen, dyspepsia/heartburn, flatulence, dizziness, headache, upper respiratory infection, taste disturbance.*Reactions that were more common in metformin hydrochloride extended-release tablets than placebo treated patients.

OVERDOSAGE

Overdose of metformin hydrochloride has occurred, including ingestion of amounts greater than 50 grams. Hypoglycemia was reported in approximately 10% of cases, but no causal association with metformin hydrochloride has been established. Lactic acidosis has been reported in approximately 32% of metformin overdose cases (see WARNINGS). Metformin is dialyzable with a clearance of up to 170 mL/min under good hemodynamic conditions. Therefore, hemodialysis may be useful for removal of accumulated drug from patients in whom metformin overdosage is suspected.

DOSAGE & ADMINISTRATION

There is no fixed dosage regimen for the management of hyperglycemia in patients with type 2 diabetes with metformin hydrochloride extended-release tablets, USP or any other pharmacologic agent. Dosage of metformin hydrochloride extended-release tablets, USP must be individualized on the basis of both effectiveness and tolerance, while not exceeding the maximum recommended daily doses. The maximum recommended daily dose of metformin hydrochloride extended-release tablets, USP in adults is 2000 mg.

Metformin hydrochloride extended-release tablets, USP should generally be given once daily with the evening meal. Metformin hydrochloride extended-release tablets, USP should be started at a low dose, with gradual dose escalation, both to reduce gastrointestinal side effects and to permit identification of the minimum dose required for adequate glycemic control of the patient.

During treatment initiation and dose titration (see Recommended Dosing Schedule), fasting plasma glucose should be used to determine the therapeutic response to metformin hydrochloride extended-release tablets, USP and identify the minimum effective dose for the patient. Thereafter, glycosylated hemoglobin should be measured at intervals of approximately 3 months. The therapeutic goal should be to decrease both fasting plasma glucose and glycosylated hemoglobin levels to normal or near normal by using the lowest effective dose of metformin hydrochloride extended-release tablets, USP either when used as monotherapy or in combination with sulfonylurea or insulin.

Monitoring of blood glucose and glycosylated hemoglobin will also permit detection of primary failure, i.e., inadequate lowering of blood glucose at the maximum recommended dose of medication, and secondary failure, i.e., loss of an adequate blood glucose lowering response after an initial period of effectiveness.

Short-term administration of metformin hydrochloride extended-release tablets, USP may be sufficient during periods of transient loss of control in patients usually well-controlled on diet alone.

Metformin hydrochloride extended-release tablets, USP must be swallowed whole and never crushed or chewed. Occasionally, the inactive ingredients of metformin hydrochloride extended-release tablets, USP will be eliminated in the feces as a soft, hydrated mass. (See Patient Informationprinted below.)

Recommended Dosing Schedule

Adults
In general, clinically significant responses are not seen at doses below 1500 mg per day. However, a lower recommended starting dose and gradually increased dosage is advised to minimize gastrointestinal symptoms.

The usual starting dose of metformin hydrochloride extended-release tablets, USP is 500 mg once daily with the evening meal. Dosage increases should be made in increments of 500 mg weekly, up to a maximum of 2000 mg once daily with the evening meal. If glycemic control is not achieved on metformin hydrochloride extended-release tablets, USP 2000 mg once daily, a trial of metformin hydrochloride extended-release tablets, USP 1000 mg twice daily should be considered. (See CLINICAL PHARMACOLOGY: Clinical Studies.)

In a randomized trial, patients currently treated with metformin hydrochloride tablets were switched to metformin hydrochloride extended-release tablets. Results of this trial suggest that patients receiving metformin hydrochloride tablets treatment may be safely switched to metformin hydrochloride extended-release tablets once daily at the same total daily dose, up to 2000 mg once daily. Following a switch from metformin hydrochloride tablets to metformin hydrochloride extended-release tablets, glycemic control should be closely monitored and dosage adjustments made accordingly (see CLINICAL PHARMACOLOGY: Clinical Studies).

Pediatrics
Safety and effectiveness of metformin hydrochloride extended-release tablets, USP in pediatric patients have not been established.

Recommendations for Use in Renal Impairment

Assess renal function prior to initiation of metformin hydrochloride extended-release tablets and periodically thereafter.
Metformin hydrochloride extended-release tablets are contraindicated in patients with an estimated glomerular filtration rate (eGFR) below 30 mL/minute/1.73 m2.
Initiation of metformin hydrochloride extended-release tablets in patients with an eGFR between 30 to 45 mL/minute/1.73 m2 is not recommended.
In patients taking metformin hydrochloride extended-release tablets whose eGFR later falls below 45 mL/min/1.73 m2, assess the benefit risk of continuing therapy.
Discontinue metformin hydrochloride extended-release tablets if the patients eGFR later falls below 30 mL/minute/1.73 m2 (See WARNINGS and PRECAUTIONS).

Discontinuation for Iodinated Contrast Imaging Procedures

Discontinue metformin hydrochloride extended-release tablets at the time of, or prior to, an iodinated contrast imaging procedure in patients with an eGFR between 30 and 60 mL/min/1.73 m2; in patients with a history of liver disease, alcoholism, or heart failure; or in patients who will be administered intra-arterial iodinated contrast. Re-evaluate eGFR 48 hours after the imaging procedure; restart metformin hydrochloride extended-release tablets if renal function is stable.

Concomitant Metformin Hydrochloride Extended-Release Tablets, USP and Oral Sulfonylurea Therapy in Adult Patients

If patients have not responded to 4 weeks of the maximum dose of metformin hydrochloride extended-release tablets monotherapy, consideration should be given to gradual addition of an oral sulfonylurea while continuing metformin hydrochloride extended-release tablets, USP at the maximum dose, even if prior primary or secondary failure to a sulfonylurea has occurred. Clinical and pharmacokinetic drug- drug interaction data are currently available only for metformin plus glyburide (glibenclamide).

With concomitant metformin hydrochloride extended-release tablets and sulfonylurea therapy, the desired control of blood glucose may be obtained by adjusting the dose of each drug. In a clinical trial of patients with type 2 diabetes and prior failure on glyburide, patients started on metformin hydrochloride tablets 500 mg and glyburide 20 mg were titrated to 1000/20 mg, 1500/20 mg, 2000/20 mg or 2500/20 mg of metformin hydrochloride tablets and glyburide, respectively, to reach the goal of glycemic control as measured by FPG, HbA1c and plasma glucose response (see CLINICAL PHARMACOLOGY: Clinical Studies). However, attempts should be made to identify the minimum effective dose of each drug to achieve this goal. With concomitant metformin hydrochloride extended-release tablets, USP and sulfonylurea therapy, the risk of hypoglycemia associated with sulfonylurea therapy continues and may be increased. Appropriate precautions should be taken. (See Package Insert of the respective sulfonylurea.)

If patients have not satisfactorily responded to 1 to 3 months of concomitant therapy with the maximum dose of metformin hydrochloride extended-release tabletsand the maximum dose of an oral sulfonylurea, consider therapeutic alternatives including switching to insulin with or without metformin hydrochloride extended-release tablets.

Concomitant Metformin Hydrochloride Extended-Release Tablets and Insulin Therapy in Adult Patients

The current insulin dose should be continued upon initiation of metformin hydrochloride extended-release tablets therapy. Metformin hydrochloride extended-release tablets therapy should be initiated at 500 mg once daily in patients on insulin therapy. For patients not responding adequately, the dose of metformin hydrochloride extended-release tablets should be increased by 500 mg after approximately 1 week and by 500 mg every week thereafter until adequate glycemic control is achieved. The maximum recommended daily dose is 2000 mg for metformin hydrochloride extended-release tablets. It is recommended that the insulin dose be decreased by 10% to 25% when fasting plasma glucose concentrations decrease to less than 120 mg/dL in patients receiving concomitant insulin and metformin hydrochloride extended-release tablets, USP. Further adjustment should be individualized based on glucose-lowering response.

Specific Patient Populations

Metformin hydrochloride extended-release tablets is not recommended for use in pregnancy. Metformin hydrochloride extended-release tablets, USP is not recommended in pediatric patients (below the age of 17 years).

The initial and maintenance dosing of metformin hydrochloride extended-release tablets should be conservative in patients with advanced age, due to the potential for decreased renal function in this population. Any dosage adjustment should be based on a careful assessment of renal function. Generally, elderly, debilitated, and malnourished patients should not be titrated to the maximum dose of metformin hydrochloride extended-release tablets.

Monitoring of renal function is necessary to aid in prevention of lactic acidosis, particularly in the elderly. (See WARNINGS.)

SPL PATIENT PACKAGE INSERT

Patient Information
Metformin Hydrochloride Extended-Release Tablets, USP
Read this information carefully before you start taking this medicine and each time you refill your prescription. There may be new information. This information does not take the place of your doctor’s advice. Ask your doctor or pharmacist if you do not understand some of this information or if you want to know more about this medicine.
What are Metformin Hydrochloride Extended-Release Tablets?
Metformin Hydrochloride Extended-Release Tablets are used to treat type 2 diabetes. This is also known as non-insulin-dependent diabetes mellitus. People with type 2 diabetes are not able to make enough insulin or respond normally to the insulin their bodies make. When this happens, sugar (glucose) builds up in the blood. This can lead to serious medical problems including kidney damage, amputations, and blindness. Diabetes is also closely linked to heart disease. The main goal of treating diabetes is to lower your blood sugar to a normal level.
High blood sugar can be lowered by diet and exercise, by a number of medicines taken by mouth, and by insulin shots. Before you take metformin hydrochloride extended-release tablets, try to control your diabetes by exercise and weight loss. While you take your diabetes medicine, continue to exercise and follow the diet advised for your diabetes. No matter what your recommended diabetes management plan is, studies have shown that maintaining good blood sugar control can prevent or delay complications of diabetes, such as blindness.
Metformin hydrochloride and Metformin hydrochloride extended-release tablets have the same active ingredient. However, metformin hydrochloride extended-release tablets works longer in your body. Both of these medicines help control your blood sugar in a number of ways. These include helping your body respond better to the insulin it makes naturally, decreasing the amount of sugar your liver makes, and decreasing the amount of sugar your intestines absorb. Metformin hydrochloride extended-release tablets do not cause your body to make more insulin. Because of this, when taken alone, they rarely cause hypoglycemia (low blood sugar), and usually do not cause weight gain. However, when they are taken with a sulfonylurea or with insulin, hypoglycemia is more likely to occur, as is weight gain.
Tell your doctor if you are pregnant or plan to become pregnant. Metformin hydrochloride extended-release tablets may not be right for you. Talk with your doctor about your choices. You should also discuss your choices with your doctor if you are nursing a child.
Can Metformin hydrochloride extended-release tablets be used in children?
Metformin hydrochloride extended-release tablets has not been studied in children.
How should I take Metformin hydrochloride extended-release tablets?
Your doctor will tell you how much medicine to take and when to take it. You will probably start out with a low dose of the medicine. Your doctor may slowly increase your dose until your blood sugar is better controlled. You should take metformin hydrochloride extended-release tablets with meals.
Your doctor may have you take other medicines along with metformin hydrochloride extended-release tablets to control your blood sugar. These medicines may include insulin shots. Taking metformin hydrochloride extended-release tablets with insulin may help you better control your blood sugar while reducing the insulin dose.
Continue your exercise and diet program and test your blood sugar regularly while taking metformin hydrochloride extended-release tablets. Your doctor will monitor your diabetes and may perform blood tests on you from time to time to make sure your kidneys and your liver are functioning normally. There is no evidence that metformin hydrochloride extended-release tablets causes harm to the liver or kidneys.
Tell your doctor if you:
• have an illness that causes severe vomiting, diarrhea or fever, or if you drink a much lower amount of liquid than normal. These conditions can lead to severe dehydration (loss of
water in your body). You may need to stop taking metformin hydrochloride extended-release tablets for a short time.
• plan to have surgery or an x-ray procedure with injection of dye (contrast agent). You may need to stop taking metformin hydrochloride extended-release tablets for a short time.
• start to take other medicines or change how you take a medicine. Metformin hydrochloride extended-release tablets can affect how well other drugs work, and some drugs can
affect how well metformin hydrochloride extended-release tablets work. Some medicines may cause high blood sugar.
Metformin hydrochloride extended-release tablets must be swallowed whole and never crushed or chewed. Occasionally, the inactive ingredients of metformin hydrochloride extended-release tablets may be eliminated as a soft mass in your stool that may look like the original tablet; this is not harmful and will not affect the way metformin hydrochloride extended-release tablets works to control your diabetes.
What should I avoid while taking Metformin hydrochloride extended-release tablets?
Do not drink a lot of alcoholic drinks while taking metformin hydrochloride extended-release tablets. This means you should not binge drink for short periods, and you should not drink a lot of alcohol on a regular basis. Alcohol can increase the chance of getting lactic acidosis.
What are the side effects of Metformin hydrochloride extended-release tablets?
• Lactic acidosis. Metformin, the active ingredient in metformin hydrochloride extended-release tablets, can cause a rare but serious condition called lactic acidosis (a
buildup of an acid in the blood) that can cause death. Lactic acidosis is a medical emergency and must be treated in the hospital.
Call your doctor right away if you have any of the following symptoms, which could be signs of lactic acidosis:
• you feel cold in your hands or feet
• you feel dizzy or lightheaded
• you have a slow or irregular heartbeat
• you feel very weak or tired
• you have unusual (not normal) muscle pain
• you have trouble breathing
• you feel sleepy or drowsy
• you have stomach pains, nausea or vomiting
Most people who have had lactic acidosis with metformin have other things that, combined with the metformin, led to the lactic acidosis. Tell your doctor if you have any of the following, because you have a higher chance for getting lactic acidosis with metformin hydrochloride extended-release tablets if you:
• have severe kidney problems, or your kidneys are affected by certain x-ray tests that use injectable dye
• have liver problems
• drink alcohol very often, or drink a lot of alcohol in short-term "binge" drinking
• get dehydrated (lose a large amount of body fluids). This can happen if you are sick with a fever, vomiting, or diarrhea. Dehydration can also happen when you sweat a lot with
activity or exercise and do not drink enough fluids
• have surgery
• have a heart attack, severe infection, or stroke
The best way to keep from having a problem with lactic acidosis from metformin is to tell your doctor if you have any of the problems in the list above. Your doctor may decide to stop your metformin hydrochloride extended-release tablets for a while if you have any of these things.
Other Side Effects. Common side effects of metformin hydrochloride extended-release tablets include diarrhea, nausea, and upset stomach. These side effects generally go away after you take the medicine for a while. Taking your medicine with meals can help reduce these side effects. Tell your doctor if the side effects bother you a lot, last for more than a few weeks, come back after they’ve gone away, or start later in therapy. You may need a lower dose or need to stop taking the medicine for a short period or for good.
About 3 out of every 100 people who take metformin hydrochloride extended-release tablets have an unpleasant metallic taste when they start taking the medicine. It lasts for a short time.
Metformin hydrochloride extended-release tablets rarely cause hypoglycemia (low blood sugar) by themselves. However, hypoglycemia can happen if you do not eat enough, if you drink alcohol or if you take other medicines to lower blood sugar.
General advice about prescription medicines
If you have questions or problems, talk with your doctor or other healthcare provider. You can ask your doctor or pharmacist for the information about metformin hydrochloride extended-release tablets that is written for healthcare professionals. Medicines are sometimes prescribed for purposes other than those listed in a patient information leaflet. Do not use metformin hydrochloride extended-release tablets for a condition for which it was not prescribed. Do not share your medicine with other people.

Dispense with Patient Information available at:
https://granulespharma.com/product/metformin-er-tab-500-750/

Manufactured by:
Granules India Limited
Hyderabad-500 081, India

Manufactured For:

Granules Pharmaceuticals Inc.

Chantilly, VA 20151.

Revision Date: 05/ 2023

HOW SUPPLIED

Metformin Hydrochloride Extended-Release Tablets, USP

500 mg Bottles of 30 NDC 70010-491-03

500 mg Bottles of 90 NDC 70010-491-09

500 mg Bottles of 100 NDC 70010-491-01

500 mg Bottles of 500 NDC 70010-491-05

500 mg Bottles of 1000 NDC 70010-491-10

750 mg Bottles of 30 NDC 70010-492-03

750 mg Bottles of 90 NDC 70010-492-09

750 mg Bottles of 100 NDC 70010-492-01

750 mg Bottles of 500 NDC 70010-492-05

750 mg Bottles of 1000 NDC 70010-492-10

Metformin Hydrochloride Extended-Release Tablets, USP 500 mg tablets are white to off-white uncoated, modified capsule shaped tablets debossed with “G7” on one side and plain on the other side.

Metformin Hydrochloride Extended-Release Tablets, USP 750 mg tablets are white to off-white uncoated, modified capsule shaped tablets debossed with “G8” on one side and plain on the other side.
Storage

Store at 20° to 25° C (68° to 77° F); excursions permitted within 15° to 30° C (59° to 86° F). [See USP Controlled Room Temperature.]

Dispense in light-resistant containers.
Dispense with Patient Information available at:
https://granulespharma.com/product/metformin-er-tab-500-750/
Manufactured by:

Granules India Limited

Hyderabad-500 081, India
Manufactured for:

Granules Pharmaceuticals Inc.

Chantilly, VA 20151.
Revision date: May 2023